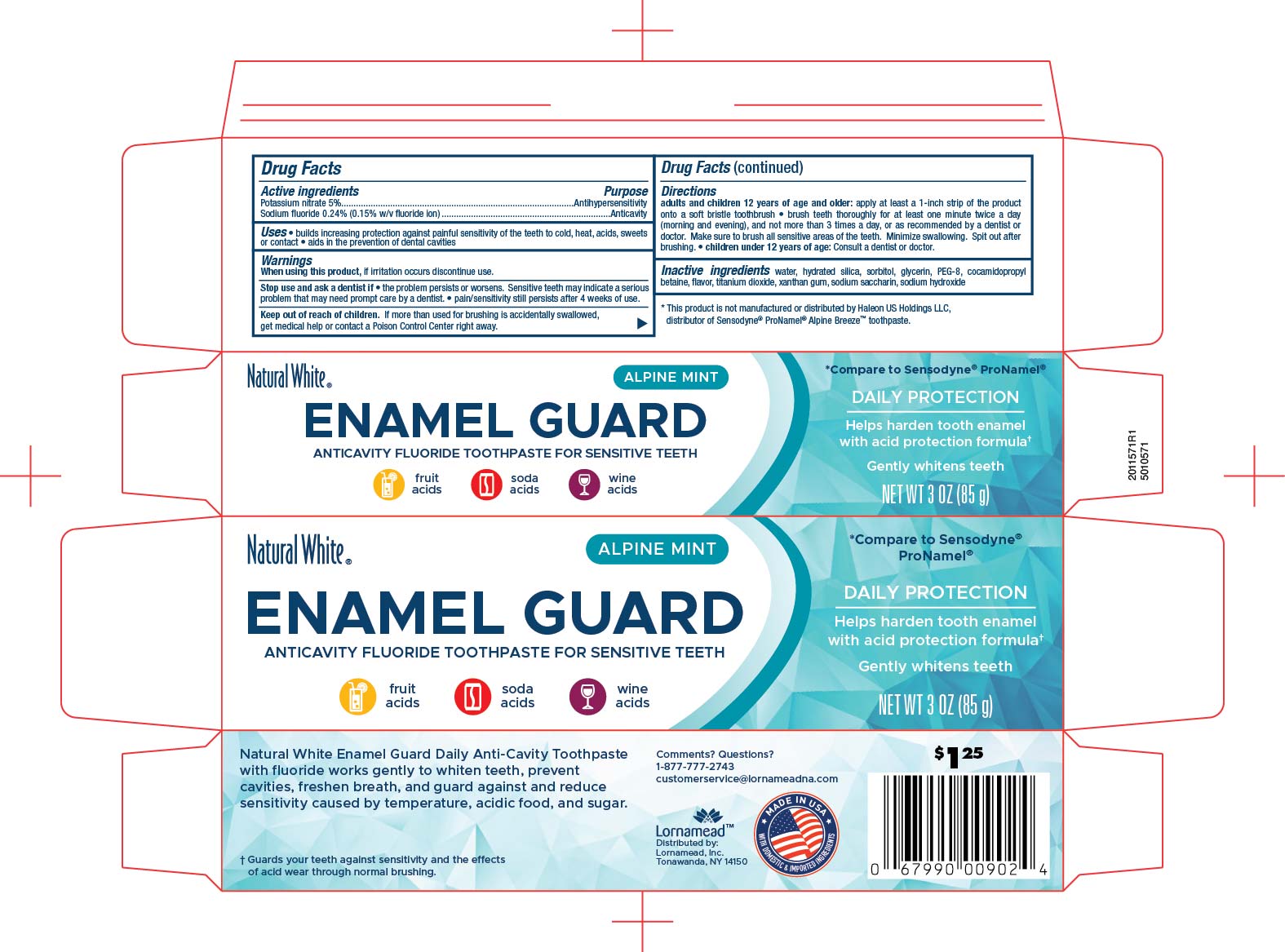 DRUG LABEL: Natural White Sensitive Enamel Guard Alpine Mint
NDC: 62721-0002 | Form: PASTE, DENTIFRICE
Manufacturer: Lornamead Products
Category: otc | Type: HUMAN OTC DRUG LABEL
Date: 20250808

ACTIVE INGREDIENTS: SODIUM FLUORIDE 0.15 g/100 g; POTASSIUM NITRATE 5 g/100 g
INACTIVE INGREDIENTS: SODIUM HYDROXIDE; HYDRATED SILICA; SODIUM SACCHARIN; XANTHAN GUM; WATER; POLYETHYLENE GLYCOL 400; TITANIUM DIOXIDE; SORBITOL; GLYCERIN; COCAMIDOPROPYL BETAINE

5010571 Dollar Tree NW Sensitive Enamel & Guard Alpine Mint (8015164)

ACTIVE INGREDIENT

Potassium nitrate 5%

Sodium fluoride 0.24% (0.15% w/v fluoride ion)

PURPOSE

Antihypersensitivity

Anticavity

Warnings

When using this product, if irritation occurs discontinue use.

Stop use and ask a dentist if

- the problem persists or worsens. Sensitive teeth may indicate a serious problem that may need prompt care by a dentist
- pain/sensitivity still persists after 4 weeks of use.

INDICATIONS AND USAGE

- builds increasing protection against painful sensitivity of the teeth to cold, heat, acids, sweets or contact
- aids in the prevention of dental cavities

KEEP OUT OF REACH OF CHILDREN

Kep out of reach of children. if more than used for brushing is accidentally swallowed, get medical help or contact a Poison Control Center right away.

INACTIVE INGREDIENT

water, hydrated silica, sorbitol, glycerin, PEG-8, cocamidopropyl betaine, flavor, titanium dioxide, xanthan gum, sodium saccharin, sodium hydroxide

Directions

adults and children 12 years of age and older: appy at least a 1-inch strip of the product onto a soft bristle toothbrush

- brush teeth thoroughly for at least one minute wice a day (morning and evening), and not more than 3 times a day, or as recommended by a dentist or doctor. Make sure to brush all sensitive areas of the teeth. Minimize swallowing. Spit out after brushing.
- children under 12 years of age: Consult a dentist or doctor.